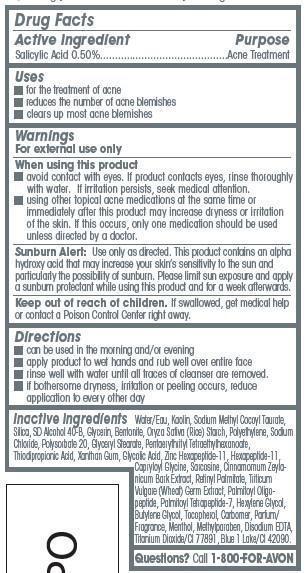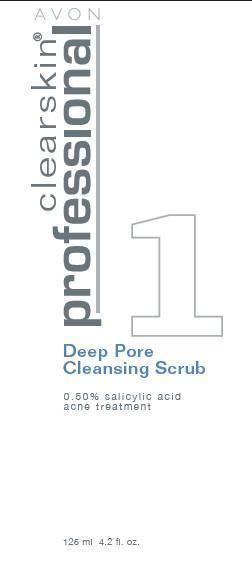 DRUG LABEL: Clearskin Professional
NDC: 10096-0155 | Form: GEL
Manufacturer: Avon Products, Inc.
Category: otc | Type: HUMAN OTC DRUG LABEL
Date: 20121111

ACTIVE INGREDIENTS: SALICYLIC ACID 5 mg/1 mL

Active ingredient
Salicylic Acid 0.50%.........................................

Purpose
..................................................Acne Treatment

Uses
• for the treatment of acne
• reduces the number of acne blemishes
• clears up most acne blemishes

Warnings
For external use only.

When using this product
• avoid contact with eyes. If product contacts eyes, rinse thoroughly with water. If irritation persists, seek medical attention.
• using other topical acne medications at the same time or immediately after this product may increase dryness or irritation of the skin. If this occurs, only one medication should be used unless directed by a doctor.

GENERAL PRECAUTIONS

Sunburn Alert: Use only as directed. This product contains an alpha hydroxy acid that may increase your skin’s sensitivity to the sun and particularly the possibility of sunburn. Please limit sun exposure and apply a sunburn protectant while using this product and for a week afterwards.

Keep out of reach of children. If swallowed, get medical help or contact a Poison Control Center right away.

Directions

- can be used in the morning and/or evening
- apply product to wet hands and rub well over entire face
- rinse well with water until all traces of cleanser are removed.
- if bothersome dryness, irritation or peeling occurs, reduce application to every other day

Inactive ingredients
Water/Eau, Kaolin, Sodium Methyl Cocoyl Taurate, Silica, SD Alcohol 40-B, Glycerin, Bentonite, Oryza Sativa (Rice) Starch, Polyethylene, Sodium Chloride, Polysorbate 20, Glyceryl Stearate, Pentaerythrityl Tetraethylhexanoate, Thiodipropionic Acid, Xanthan Gum, Glycolic Acid, Zinc Hexapeptide-11, Hexapeptide-11, Capryloyl Glycine, Sarcosine, Cinnamomum Zeylanicum Bark Extract, Retinyl Palmitate, Triticum Vulgare (Wheat) Germ Extract, Palmitoyl Oligopeptide, Palmitoyl Tetrapeptide-7, Hexylene Glycol, Butylene Glycol, Tocopherol, Carbomer, Parfum/Fragrance, Menthol, Methylparaben, Disodium EDTA, Titanium Dioxide/CI 77891, Blue 1 Lake/CI 42090.

Questions? Call 1-800-FOR-AVON